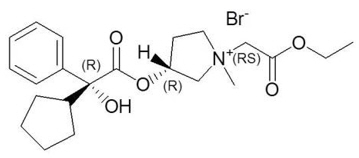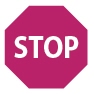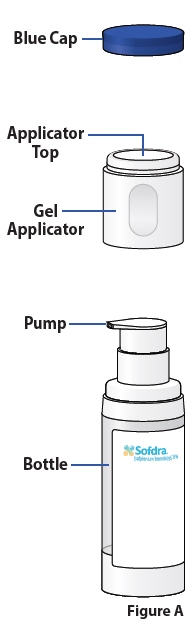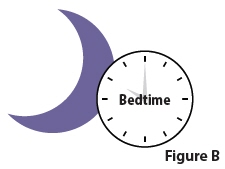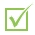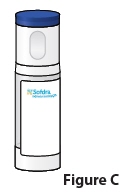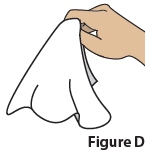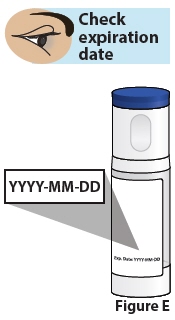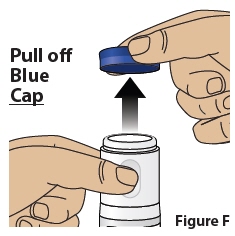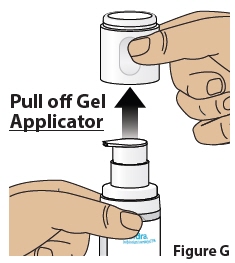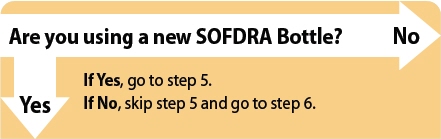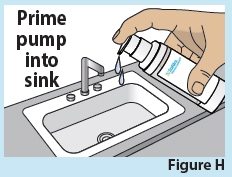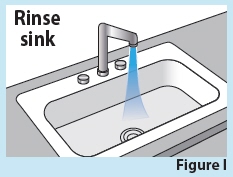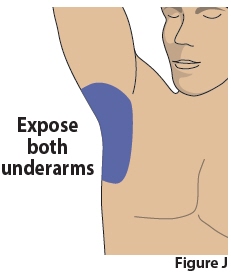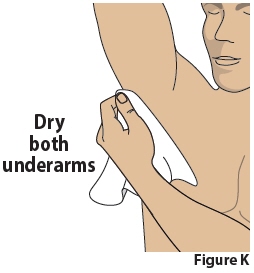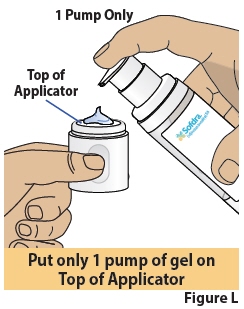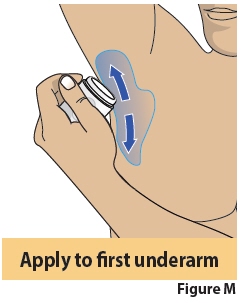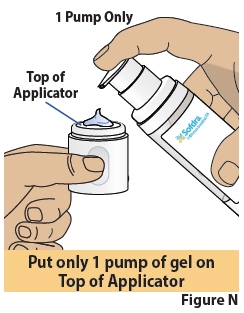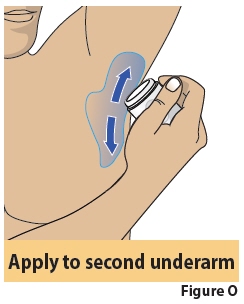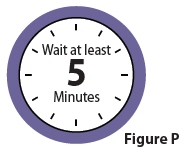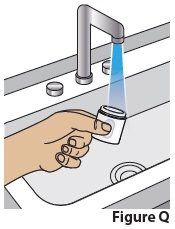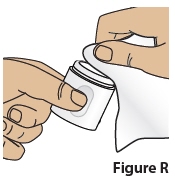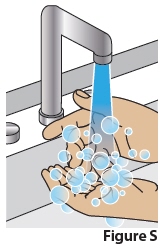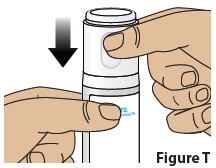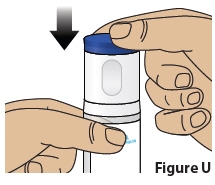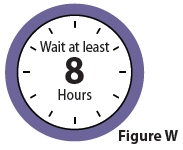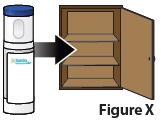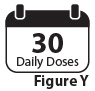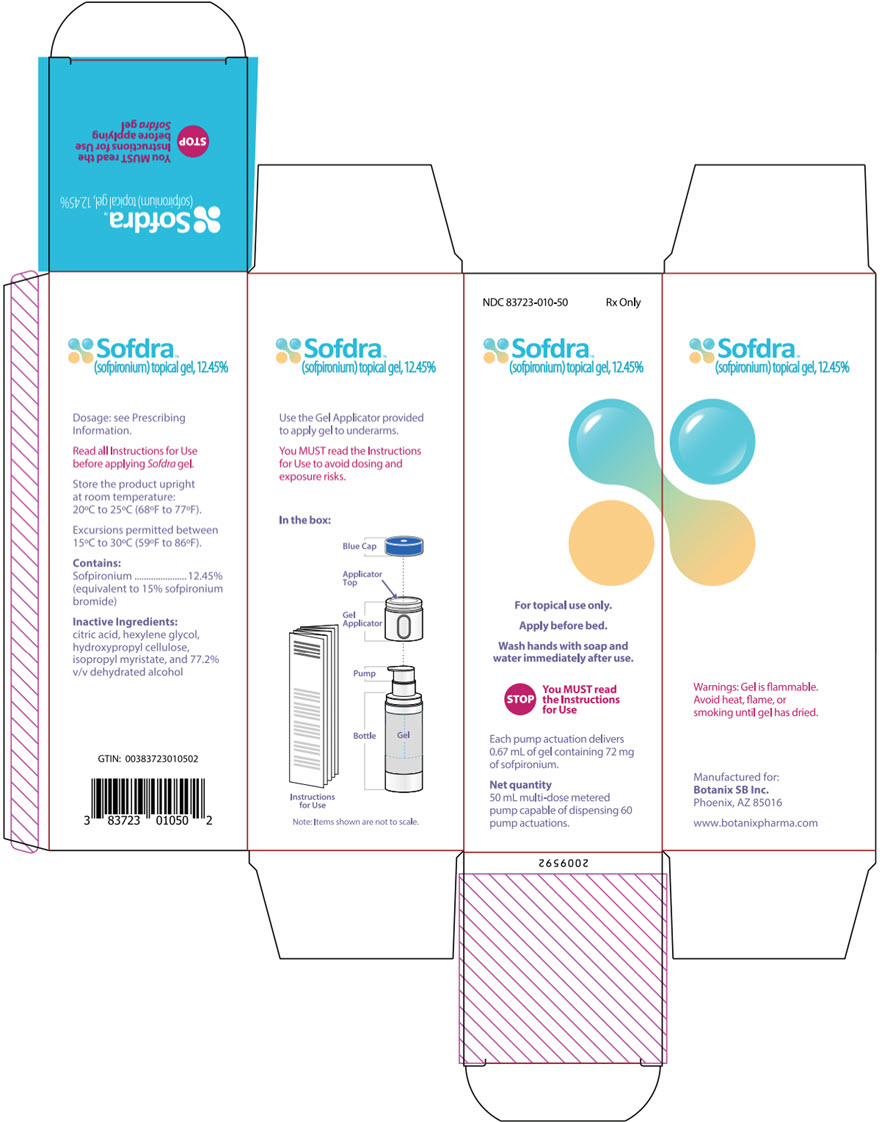 DRUG LABEL: Sofdra
NDC: 83723-010 | Form: GEL
Manufacturer: Botanix SB Inc.
Category: prescription | Type: HUMAN PRESCRIPTION DRUG LABEL
Date: 20250922

ACTIVE INGREDIENTS: SOFPIRONIUM BROMIDE 87 mg/0.67 mL
INACTIVE INGREDIENTS: HEXYLENE GLYCOL; ISOPROPYL MYRISTATE; HYDROXYPROPYL CELLULOSE, UNSPECIFIED; CITRIC ACID MONOHYDRATE; ALCOHOL

HIGHLIGHTS OF PRESCRIBING INFORMATION

These highlights do not include all the information needed to use SOFDRA™ safely and effectively. See full prescribing information for SOFDRA.
SOFDRA (sofpironium) topical gel, 12.45%
Initial U.S. Approval: 2024

1 INDICATIONS AND USAGE

SOFDRA is an anticholinergic indicated for the treatment of primary axillary hyperhidrosis in adults and pediatric patients 9 years of age and older (1).

2 DOSAGE AND ADMINISTRATION

Apply 1 pump of SOFDRA per underarm once a day at bedtime. For topical use only (2).

3 DOSAGE FORMS AND STRENGTHS

Topical gel: 12.45% of sofpironium (3).

4 CONTRAINDICATIONS

Medical conditions that can be exacerbated by the anticholinergic effect of SOFDRA (e.g., glaucoma, paralytic ileus, unstable cardiovascular status in acute hemorrhage, severe ulcerative colitis, toxic megacolon complicating ulcerative colitis, myasthenia gravis, Sjögren's syndrome) (4).

5 WARNINGS AND PRECAUTIONS

- Urinary Retention:Use with caution in patients with a history or presence of documented urinary retention. Discontinue use immediately and consult a healthcare provider should any signs or symptoms of urinary retention develop (5.1).
- Control of Body Temperature:Watch for generalized lack of sweating when in hot or very warm environmental temperatures and avoid using SOFDRA if not sweating under these conditions (5.2).
- Operating Machinery or an Automobile:Transient blurred vision may occur with use of SOFDRA. If blurred vision occurs, discontinue use and avoid operating a motor vehicle or other machinery until symptoms resolve (5.3).

6 ADVERSE REACTIONS

Most common adverse reactions (incidence ≥2%) are dry mouth, vision blurred, application site pain, application site erythema, mydriasis, application site dermatitis, application site pruritus, urinary retention, and application site irritation (6.1).

To report SUSPECTED ADVERSE REACTIONS, contact Botanix SB Inc. at 1-866-763-6337 or FDA at 1-800-FDA-1088 or www.fda.gov/medwatch.

7 DRUG INTERACTIONS

- Anticholinergics:Coadministration of SOFDRA with anticholinergic medications may result in additive interaction leading to an increase in anticholinergic adverse effects. Avoid coadministration of SOFDRA with other anticholinergic-containing drugs (7.1).
- Strong Inhibitors of CYP2D6:Avoid co-administration of SOFDRA with drugs that are strong inhibitors of CYP2D6 (7.2).

FULL PRESCRIBING INFORMATION

1 INDICATIONS AND USAGE

SOFDRA is indicated for the treatment of primary axillary hyperhidrosis in adults and pediatric patients 9 years of age and older.

2 DOSAGE AND ADMINISTRATION

- Do not shave armpits at least 8 hours before applying SOFDRA.
- Do not shower at least 30 minutes before applying SOFDRA.
- Apply SOFDRA to clean, dry skin once a day at bedtime.
- Apply a single pump actuation to the top of the supplied applicator. Spread the entire amount to cover 1 underarm. Apply a separate, single pump actuation to the top of the supplied applicator. Apply the entire amount to the second underarm. Allow to dry completely (5 minutes) before putting on clothing.
- Wash hands immediately with soap.
- For topical use only.
- Avoid fire, flame, and smoking during and immediately following application.
- Do not shower or wash underarms for at least 8 hours after application.
- Do not touch underarms after applying SOFDRA.
- Do not use more than once daily.
- Avoid transfer of SOFDRA to the periocular area [see Warnings and Precautions (5.3)] .
- Do not apply SOFDRA to broken skin.
- Avoid using SOFDRA with occlusive dressings.

3 DOSAGE FORMS AND STRENGTHS

Topical gel: 12.45% (w/w) of sofpironium in a 50 mL bottle with a metered dose pump and applicator. One full pump delivers 72 mg sofpironium in 0.67 mL of gel.

4 CONTRAINDICATIONS

SOFDRA is contraindicated in patients with medical conditions that can be exacerbated by the anticholinergic effect of sofpironium bromide (e.g., glaucoma, paralytic ileus, unstable cardiovascular status in acute hemorrhage, severe ulcerative colitis, toxic megacolon complicating ulcerative colitis, myasthenia gravis, Sjögren's syndrome).

5 WARNINGS AND PRECAUTIONS

5.1 Urinary Retention

Use SOFDRA with caution in patients with a history or presence of documented urinary retention. Prescribers and patients should be alert for signs and symptoms of urinary retention (e.g., difficulty passing urine, distended bladder), especially in patients with prostatic hypertrophy or bladder-neck obstruction. Discontinue use immediately and consult a healthcare provider should any of these signs or symptoms develop.

5.2 Control of Body Temperature

In the presence of high ambient temperature, heat illness (hyperpyrexia and heat stroke due to decreased sweating) can occur with the use of anticholinergic drugs, including SOFDRA. Watch for generalized lack of sweating when in hot or very warm environmental temperatures and avoid using SOFDRA if not sweating under these conditions.

5.3 Operating Machinery or an Automobile

Transient blurred vision may occur with use of SOFDRA. If blurred vision occurs, discontinue use and avoid engaging in activities that require clear vision, such as operating a motor vehicle or other machinery or performing hazardous work, until the symptoms have resolved.

6 ADVERSE REACTIONS

The following clinically significant adverse reactions are described elsewhere in the labeling:

Urinary Retention [See Warnings and Precautions (5.1)].

6.1 Clinical Trials Experience

Because clinical trials are conducted under widely varying conditions, adverse reaction rates observed in the clinical trials of a drug cannot be directly compared to rates in the clinical trials of another drug and may not reflect the rates observed in practice.

In two double-blind, vehicle controlled clinical trials (CARDIGAN 1 and CARDIGAN 2) of 700 subjects 10 to 76 years of age (353 subjects treated with SOFDRA and 347 subjects treated with vehicle), 44% of subjects were male, 79% were White, 21% were Black, and 1% were Asian. A total of 618 subjects completed at least 6 weeks of treatment, including 307 subjects treated with SOFDRA and 311 subjects treated with vehicle.

Table 1 summarizes the most frequent adverse reactions (≥2%) in subjects with primary axillary hyperhidrosis treated with SOFDRA.

Table 1: Adverse Reactions Occurring in ≥2% of Subjects with Primary Axillary Hyperhidrosis Treated with SOFDRA in Trials CARDIGAN 1 and 2
Adverse Reactions | SOFDRA (N = 353) n (%) | Vehicle (N = 347) n (%)
Dry mouth | 51 (14%) | 2 (0.6%)
Vision blurred | 30 (9%) | 1 (0.3%)
Mydriasis | 23 (7%) | 0
Urinary retention | 8 (2%) | 0
Note: COVID-19 was observed in 8 (2%) SOFDRA and 2 (0.6%) vehicle subjects.

Table 2 shows the local skin reactions reported ≥2%, which occurred more commonly in the SOFDRA group.

Table 2: Local Skin Reactions Reported in ≥2% of Subjects with Primary Axillary Hyperhidrosis Treated with SOFDRA in Trials CARDIGAN 1 and 2
Local Skin Adverse Reactions | SOFDRA (N = 353) n (%) | Vehicle (N = 347) n (%)
Pain | 29 (8%) | 6 (2%)
Erythema | 23 (7%) | 1 (0.3%)
Dermatitis | 21 (6%) | 1 (0.3%)
Pruritus | 16 (5%) | 2 (0.6%)
Irritation | 8 (2%) | 1 (0.3%)
Exfoliation | 7 (2%) | 1 (0.3%)

In an open-label, long-term safety trial (ARGYLE), 197 subjects were treated for 48 weeks with SOFDRA. Adverse reactions occurring at a frequency ≥2% were vision blurred (19%), dry mouth (17%), application site pruritus (15%), application site pain (15%), application site dermatitis (11%), application site erythema (8%), application site irritation (6%), mydriasis (5%), application site rash (4%), upper respiratory tract infection (4%), dry eye (4%), urinary retention (4%), application site exfoliation (3%), application site folliculitis (3%), hypertension (3%), application site dryness (2%), viral upper respiratory tract infection (2%), influenza (2%), and headache (2%).

7 DRUG INTERACTIONS

7.1 Anticholinergics

Coadministration of SOFDRA with anticholinergic medications may result in additive interaction leading to an increase in anticholinergic adverse effects [See Warnings and Precautions (5.2)and Adverse Reactions (6.1)] . Avoid coadministration of SOFDRA with other anticholinergic-containing drugs.

7.2 Strong Inhibitors of CYP2D6

Avoid co-administration of SOFDRA with drugs that are strong inhibitors of CYP2D6.

8 USE IN SPECIFIC POPULATIONS

8.1 Pregnancy

Risk Summary

There are no available data with SOFDRA use in pregnant women to evaluate for drug-associated risks of major birth defects, miscarriage or adverse maternal or fetal outcomes. In animal reproduction studies, subcutaneous administration of sofpironium bromide to pregnant rats and rabbits during the period of organogenesis resulted in no significant adverse effects at doses 31 and 10 times, respectively, the maximum recommended human dose (MRHD) (see Data).

The background risks of major birth defects and miscarriage for the indicated population are unknown. All pregnancies have a background risk of birth defects, loss, and other adverse outcomes. In the U.S. general population, the estimated background risk of major birth defects and miscarriage in clinically recognized pregnancies is 2-4% and 15-20%, respectively.

Data

Animal Data

In an embryofetal development study in rats, sofpironium bromide was not associated with embryofetal lethality or fetal malformations at subcutaneous dose levels of 1, 3, and 10 mg/kg/day administered during the period of organogenesis. The maternal and fetal survival, growth and development no observed adverse effect level (NOAEL) was 10 mg/kg/day (31 times the MRHD based on AUC comparisons).

In an embryofetal development study in rabbits, sofpironium bromide was administered by subcutaneous injection to pregnant rabbits at doses of 0.4, 2 and 10 mg/kg/day during the period of organogenesis. Maternal toxicity as evidenced by decreased maternal body weight gain and feed consumption was observed in all sofpironium bromide treated groups. The decrease in maternal body weight was considered severe at 10 mg/kg/day and was associated with embryofetal lethality. The maternal toxicity NOAEL could not be established in the study. The NOAEL for embryo-fetal development toxicity was 2 mg/kg/day (10 times the MRHD based on AUC comparison). Fetal malformation was not observed with sofpironium bromide treatment at doses up to 10 mg/kg/day (57 times the MRHD based on AUC comparison) in rabbits.

In a pre- and postnatal development study, sofpironium bromide was administered by subcutaneous injection to pregnant rats at doses of 1, 3 and 6 mg/kg/day beginning on gestation day 6 through lactation day 20. Maternal toxicity associated with a 17% decrease in body weight gain noted at 6 mg/kg/day (approximately 19 times the MRHD based on AUC comparisons) when compared to the control group. No sofpironium bromide-related effects on prenatal and postnatal development, neurobehavioral or reproductive performance of offspring were noted at doses up to 6 mg/kg/day (approximately 19 times the MRHD based on AUC comparison).

8.2 Lactation

Risk Summary

There are no data on the presence of SOFDRA or its metabolites in human milk, the effects on the breastfed infant, or the effects on milk production. The developmental and health benefits of breastfeeding should be considered along with the mother's clinical need for SOFDRA and any potential adverse effects on the breastfed infant from sofpironium bromide or from the underlying maternal condition.

Sofpironium bromide was detected in milk following single subcutaneous administration to lactating rats (see Data). When a drug is present in animal milk, it is likely that the drug will be present in human milk.

Data

Animal Data

Milk excretion studies in vivo showed sofpironium or its metabolites were transferred into the milk after a single subcutaneous administration of 0.5 mg/kg to lactating rats on postnatal day 10.

8.4 Pediatric Use

The safety, effectiveness, and pharmacokinetics of SOFDRA for the treatment of primary axillary hyperhidrosis have been established in pediatric patients 9 years of age and older [See Clinical Pharmacology (12.3)] . Use of SOFDRA in this age group is supported by evidence from two multicenter, randomized, double-blind, parallel-group, vehicle-controlled 6-week trials and two multicenter, open-label, 24-week and 48-week trials, which included 72 pediatric subjects 9 years of age and older [See Adverse Reactions (6.1)and Clinical Studies (14)] .

The safety and effectiveness of SOFDRA have not been established in pediatric patients younger than 9 years of age.

8.5 Geriatric Use

Clinical trials of SOFDRA did not include sufficient numbers of subjects aged 65 years and older to determine whether they respond differently from younger subjects. Other reported clinical experience has not identified differences in responses between the elderly and younger patients.

In general, dose selection for an elderly patient should be cautious, usually starting at the low end of the dosing range, reflecting the greater frequency of decreased hepatic, renal, or cardiac function and of concomitant disease or other drug therapy.

8.6 Renal Impairment

The safety and effectiveness of SOFDRA in populations with renal impairment have not been established.

8.7 Hepatic Impairment

The safety and effectiveness of SOFDRA in populations with hepatic impairment have not been established.

10 OVERDOSAGE

In case of an overdose, remove the topically applied product with soap and water, and treat the symptoms and signs attributed to the overdose symptomatically. Consider contacting the Poison Center at 1-800-222-1222 for the latest recommendations.

11 DESCRIPTION

SOFDRA (sofpironium) topical gel is an anticholinergic drug. Sofpironium bromide drug substance is a white to off white powder with the chemical name 3'(R)-[2(R) cyclopentylphenylhydroxy-acetoxy]-1'-methyl-1'-ethoxycarbonylmethyl-pyrrolidinium bromide, very soluble in chloroform and freely soluble in water, ethanol, acetonitrile, and methanol, molecular formula of C22H32BrNO5, molecular weight of 470.4 g/mol, and the following structural formula:

SOFDRA is a clear to translucent, colorless to pale yellow viscous gel containing 12.45% (w/w) sofpironium (equivalent to 15% sofpironium bromide) in an airless bottle sealed with a multi-dose metered pump. Each pump delivers 72 mg of sofpironium (equivalent to 87 mg of sofpironium bromide) in 0.67 mL of gel. The inactive ingredients are citric acid, 77.2% v/v dehydrated alcohol, hexylene glycol, hydroxypropyl cellulose, and isopropyl myristate.

12 CLINICAL PHARMACOLOGY

12.1 Mechanism of Action

Sofpironium bromide is a competitive inhibitor of acetylcholine receptors that are located on certain peripheral tissues, including sweat glands. Sofpironium bromide indirectly reduces the rate of sweating by preventing the stimulation of these receptors.

12.2 Pharmacodynamics

Pharmacodynamics of SOFDRA are unknown.

Cardiac Electrophysiology

At an exposure 3 times the exposure associated with the maximum approved recommended dose, SOFDRA does not prolong the QTc interval to any clinically relevant extent.

12.3 Pharmacokinetics

Absorption

The pharmacokinetics of sofpironium were evaluated in adult patients with primary axillary hyperhidrosis following SOFDRA applied once daily to the underarms for 21 days. The mean ± standard deviation (SD) exposures of sofpironium in adults are presented in Table 3. There was no evidence of accumulation.

Table 3: Mean (SD) Plasma Exposure of Sofpironium in Adults with Primary Axillary Hyperhidrosis Following SOFDRA Application on Day 1
PK Parameter | Adult Patients
Cmax(ng/mL) | 2.71 (6.94)
AUC0-t(ng∙hr/mL) | 45.1 (85.1)
tmax(hr) | 5.34 (5.45)

Distribution

Plasma protein binding of sofpironium is around 34.8-37.8%. The major sofpironium metabolite (BBI-4010) had plasma protein binding around 2.3-3.7%.

Elimination

Metabolism

Sofpironium is metabolized by nonenzymatic hydrolysis, CYP2D6 and CYP3A4 mediated-oxidative metabolism, and glycine conjugation. In plasma, sofpironium was the major component (38%) followed by the BBI-4010 (20%) metabolite.

Excretion

Urinary excretion of sofpironium and BBI-4010 were less than 0.5% of the applied dose.

Specific Populations

The pharmacokinetics of sofpironium were not evaluated in pregnant patients or patients with hepatic or renal impairment.

Pediatric Subjects

The mean ± SD exposures of sofpironium after a single dose in pediatric subjects 9 years to 16 years of age are presented in Table 4. After 24 weeks of dosing, trough concentrations of sofpironium were low and there was no evidence of accumulation. The exposure to major metabolite (BBI-4010) in pediatric subjects was similar to sofpironium exposure in adults.

Table 4: Mean (SD) Plasma Exposure of Sofpironium in Pediatric Subjects Following Single Dose Administration of SOFDRA on Day 1
PK Parameter | Pediatric Patients
Cmax(ng/mL) | 1.30 (3.16)
AUC0-t(ng∙hr/mL) | 14.6 (35.0)
tmax(hr) | 4.0 (0.9, 23.1)
tmaxreported as median and range.

Drug Interaction Studies

No clinically significant differences in sofpironium pharmacokinetics were observed when used concomitantly with inhibitors of CYP3A4, OCT2, MATE1, or MATE2-K.

In vivo Study

In presence of 20 mg oral dose of paroxetine HCl (strong CYP2D6 inhibitor) Cmaxand AUC0-tof sofpironium increased by approximately twofold compared to when SOFDRA was administered alone.

In vitro Studies

Sofpironium is an inhibitor of CYP2D6, CYP3A4, OCT1, OCT2, and MATE1 in vitro. Sofpironium is not an inducer of CYP1A2, CYP2B6, or CYP3A4.

13 NONCLINICAL TOXICOLOGY

13.1 Carcinogenesis, Mutagenesis, Impairment of Fertility

The carcinogenic potential of sofpironium bromide was assessed in a 2-year dermal mouse carcinogenicity study and a 2-year subcutaneous rat carcinogenicity study. There were no drug-related neoplasms associated with daily topical administration of sofpironium bromide topical gel to mice at doses of up to 20% sofpironium bromide (2 times and 11 times the MRHD based on AUC comparisons for males and females, respectively). No drug-related neoplasms were identified in rats administered daily subcutaneous doses up to 1.5 mg/kg/day (males) and 5.0 mg/kg/day (females) (4 times and 12 times the MRHD based on AUC comparisons for males and females, respectively).

Sofpironium bromide was not mutagenic in a bacterial mutagenicity assay (Ames assay) or clastogenic in an in vitro mammalian chromosomal aberration assay (human peripheral blood lymphocytes) or in an in vivo micronucleus assay in rats.

There were no sofpironium bromide-related effects on male or female fertility and early embryonic developmental endpoints in rats at subcutaneous doses up to 10 mg/kg/day (70 and 20 times the MRHD based on AUC comparisons for males and females, respectively).

14 CLINICAL STUDIES

Two randomized, vehicle-controlled multicenter trials, CARDIGAN 1 (NCT03836287) and CARDIGAN 2 (NCT03948646), enrolled a total of 701 subjects 10 years of age or older with primary axillary hyperhidrosis. All subjects were to have symptoms of axillary hyperhidrosis for at least 6 months' duration, produce at least 50 mg of sweat in each axilla (underarm) with a combined total of at least 150 mg over a 5-minute period, and have a Hyperhidrosis Disease Severity Measure-Axillary, 7-item scale score (HDSM-Ax-7) ≥3.

In the trials, 56% of subjects were female, 78% were White, and 20% were Black or African American; for ethnicity, 31% identified as Hispanic or Latino. Fewer than 1% of subjects were less than 12 years of age, 7% were 12 to 17 years of age, 91% were 18 to 64 years of age, and 1% were 65 years of age or older.

Subjects 12 years of age and older were asked to rate their underarm sweating severity and frequency since waking on the previous day ("since you woke up yesterday") on the 11-item HDSM-Ax Adult version instrument. The HDSM-Ax-7 scale score was calculated by taking an average of 7 items, where the scale score ranges from 0 to 4 with a higher score representing greater underarm sweating severity. The mean HDSM-Ax-7 scale score at Baseline was 3.5 in CARDIGAN 1, and 3.6 in CARDIGAN 2. The median gravimetric sweat production (GSP) over 5 minutes at Baseline was 214.1 mg in the SOFDRA arm and 228.6 mg in the vehicle arm in CARDIGAN 1, and 207.7 mg in the SOFDRA arm and 231.1 mg in the vehicle arm in CARDIGAN 2.

Subjects were randomized to receive either SOFDRA or vehicle applied once daily at bedtime to each axilla. The co-primary endpoints were the proportion of subjects having at least a 2-point improvement in the HDSM-Ax-7 scale score from Baseline to Day 43, and the change in GSP from Baseline to Day 43.

The results of CARDIGAN 1 and CARDIGAN 2 are presented in Table 5.

Table 5: Primary Efficacy Endpoints at Day 43 in Subjects with Primary Axillary Hyperhidrosis in Trials CARDIGAN 1 and 2
 | CARDIGAN 1 |  | CARDIGAN 2
 | SOFDRA | Vehicle | SOFDRA | Vehicle
≥2 point Improvement in HDSM-Ax-7 [Hyperhidrosis Disease Severity Measure-Axillary, 7-item score] scale score from Baseline to Day 43 in subjects 12 years of age and older | N = 172 49% | N= 177 29% | N = 178 64% | N = 169 48%
Treatment Difference 95% Confidence Interval | 18% (8%, 29%) |  | 17% (6%, 27%)
Baseline Median GSP [Gravimetric Sweat Production] in subjects 10 years of age and older (mg/5 minutes) | N = 173 214 | N = 177 229 | N = 180 208 | N = 171 231
Change from Baseline to Day 43 Median (mg/5 minutes) 25thpercentile, 75thpercentile | -128 -201, -52 | -100 -228, -29 | -143 -260, -75 | -134 -230, -60

16 HOW SUPPLIED/STORAGE AND HANDLING

How Supplied

SOFDRA topical gel is supplied in a bottle with a multi-dose metered pump, applicator, and cap. Each bottle contains 50 mL of gel with a multi-dose pump capable of dispensing 60 pump actuations. Each pump actuation dispenses 0.67 mL of gel.

NDC 83723-010-50

Storage and Handling

Store upright at 20°C to 25°C (68°F to 77°F); excursions permitted to 15°C to 30°C (59°F to 86°F) [See USP Controlled Room Temperature].

SOFDRA is flammable; keep away from heat or flame.

17 PATIENT COUNSELING INFORMATION

Advise the patient to read the FDA-approved patient labeling (Patient Information and Instructions for Use).

Urinary Retention

Instruct patients to be alert for signs and symptoms of urinary retention (e.g., difficulty passing urine, distended bladder). Instruct patients to discontinue use and consult a healthcare provider immediately should any of these signs or symptoms develop [see Warnings and Precautions (5.1)] .

Control of Body Temperature

Advise patients that in the presence of high ambient temperature, heat illness due to decreased sweating can occur with the use of SOFDRA. Advise patients to watch for generalized lack of sweating when in hot or very warm environmental temperatures and to avoid using SOFDRA if not sweating under these conditions [see Warnings and Precautions (5.2)] .

Operating Machinery or an Automobile

Advise patients that transient blurred vision may occur with SOFDRA. If this occurs, instruct patients to contact their healthcare provider, discontinue use of SOFDRA, and avoid operating a motor vehicle or other machinery or performing hazardous work until symptoms resolve [see Warnings and Precautions (5.3)] .

Instructions for Administering SOFDRA

Advise patients as follows [see Dosage and Administration (2)] :

- Do not shave armpits at least 8 hours before applying SOFDRA.
- Do not shower at least 30 minutes before applying SOFDRA.
- Apply 1 pump actuation per underarm to clean, dry skin once a day at bedtime (total 2 pumps). Allow to dry completely (5 minutes) before putting on clothing.
- Wait at least 8 hours after applying the gel to shower or wash underarms.
- Do not use SOFDRA more frequently than once daily.
- Instruct patients to wash their hands with soap and water immediately after applying SOFDRA.
- Instruct patients not to apply SOFDRA to other body areas or to broken skin and to avoid using SOFDRA with occlusive dressings.
- SOFDRA is flammable; avoid fire, flame, and smoking during and immediately following application.

Manufactured for:
Botanix SB Inc.
Phoenix, AZ 85016

PATIENT INFORMATION
SOFDRA™ (sof-drah)
(sofpironium)
topical gel, 12.45%

Important information: SOFDRA is for use on the skin in the underarm area only. Do not apply SOFDRA to other parts of your body.

What is SOFDRA?
SOFDRA is a prescription anticholinergic medicine used on the skin (topical) to treat excessive underarm sweating (primary axillary hyperhidrosis) in adults and children 9 years of age and older.
It is not known if SOFDRA is safe and effective in children under 9 years of age.

Who should not use SOFDRA?
Do not use SOFDRA if you have certain medical conditions that can be made worse by taking an anticholinergic medicine such as:

- glaucoma
- severe ulcerative colitis or certain other serious bowel problems
- myasthenia gravis
- Sjögren's syndrome

Talk to your healthcare provider if you are not sure if you have a medical condition that can be made worse by taking an anticholinergic medicine.

Before using SOFDRA, tell your healthcare provider about all of your medical conditions, including if you:

- have prostate or bladder problems, or problems passing urine
- have kidney problems
- are pregnant or plan to become pregnant. It is not known if SOFDRA will harm your unborn baby.
- are breastfeeding or plan to breastfeed. It is not known if SOFDRA passes into your breast milk. Talk to your healthcare provider about the best way to feed your baby during treatment with SOFDRA.

Tell your healthcare provider about all the medicines you take,including prescription medicines, over-the-counter medicines, vitamins, and herbal supplements.
SOFDRA may affect the way other medicines work causing side effects. Especially tell your healthcare provider if you take anticholinergic medicines.
Know the medicines you take. Keep a list of your medicines with you and show it to your healthcare provider and pharmacist when you get a new medicine.

How should I use SOFDRA?

- Use SOFDRA exactly as your healthcare provider tells you to use it.
- See the detailed " Instructions for Use" for directions about how to apply SOFDRA.
- Apply SOFDRA 1 time a day at bedtime.
- Apply SOFDRA to clean, dry, intact skin of your underarm areas only.
- Apply SOFDRA to both underarm areas using 1 pump for each underarm.
- Do notshower or wash underarms for at least 8 hours after applying SOFDRA.
- Do notuse SOFDRA more than 1 time a day.
- Do notapply SOFDRA to broken skin.
- Do notcover the treated area with a plastic (occlusive) dressing.
- Do notapply SOFDRA if you have shaved your underarms or applied deodorant within the last 8 hours.
- Do notapply SOFDRA if you have exercised or showered or washed your underarms within the last 30 minutes.
- Wash your hands with soap and water right away after you apply SOFDRA.It is important that you wash your hands because the SOFDRA that is still on your hands can cause you to have blurred vision if you touch your eyes.
- Do not allow clothing to contact SOFDRA for 5 minutes after applying.
- Do not touch your underarms after applying SOFDRA.
- If you use too much SOFDRA, remove SOFDRA with soap and water, and call your healthcare provider or Poison Help line at 1-800-222-1222.

What should I avoid while using SOFDRA?

- SOFDRA may cause you to have blurred vision that is temporary. If you develop blurred vision, call your healthcare provider, stop using SOFDRA and do not drive, operate machinery, or do hazardous work until your vision is clear.
- SOFDRA is flammable.Avoid fire, flame, and smoking during and right after applying SOFDRA to your skin.

What are possible side effects of SOFDRA?
SOFDRA can cause serious side effects, including:

- Urinary retention.People who use SOFDRA may develop urinary retention. Symptoms of urinary retention may include:
  - difficulty urinating
  - urinating frequently
  - urination in a weak stream or drips
  - full bladder or difficulty emptying your bladder (distended bladder)
  If you develop these symptoms, stop using SOFDRA and call your healthcare provider right away.
- Problems with control of your body temperature.SOFDRA can cause you to have decreased sweating in areas of your body other than the underarm area which could cause you to become overheated and to develop heat illness. When in hot or very warm temperatures, watch for lack of sweating on your body and stop using SOFDRA if you develop lack of sweating on your body. Stop using SOFDRA and call your healthcare provider right away if you develop any of these symptoms of heat illness:
  - hot, red skin
  - decreased alertness or passing out (unconsciousness)
  - fast, weak pulse
  - fast, shallow breathing
  - increased body temperature (fever)
- Blurred vision.See " What should I avoid while using SOFDRA?"

The most common side effects of SOFDRA include:

- dry mouth
- blurred vision
- pain, redness, swelling, itching and irritation in the underarm area
- dilation of the pupils of your eyes (mydriasis)
- problems with urination

These are not all of the possible side effects of SOFDRA.
Call your doctor for medical advice about side effects. You may report side effects to FDA at 1-800-FDA-1088.

How should I store SOFDRA?

- Store SOFDRA upright at room temperature between 68°F to 77°F (20°C to 25°C).
- SOFDRA is flammable.Keep SOFDRA away from heat or flame.

Keep SOFDRA and all medicines out of the reach of children.

General information about the safe and effective use of SOFDRA.
Medicines are sometimes prescribed for purposes other than those listed in a Patient Information leaflet. Do not use SOFDRA for a condition for which it was not prescribed. Do not give SOFDRA to other people, even if they have the same condition you have. You can ask your pharmacist or healthcare provider for information about SOFDRA that is written for healthcare professionals.

What are the ingredients in SOFDRA?
Active ingredient: sofpironium
Inactive ingredients:citric acid, dehydrated alcohol, hexylene glycol, hydroxypropyl cellulose, and isopropyl myristate.
Manufactured for:
Botanix SB Inc., Phoenix, AZ 85016
For more information, go to www.sofdra.com or call 1-866-763-6337

This Patient Information has been approved by the U.S. Food and Drug Administration.

Issued: 07/2025

INSTRUCTIONS FOR USE

SOFDRA™
(sof-drah)
(sofpironium)
topical gel, 12.45%

These Instructions for Use contain information on how to use SOFDRA.

Read the Instructions for Use before you start using SOFDRA and each time you get a refill.

This information does not take the place of talking to your healthcare provider about your medical condition or your treatment.

If you have questions, ask your pharmacist or healthcare provider.

SOFDRA Parts

Important Information You Need to Know Before Applying SOFDRA

- SOFDRA gel should be used before bedtime.
- SOFDRA gel is for the underarms only. Do notapply SOFDRA to any other part of the body. Do notapply SOFDRA to broken skin.
- One complete dose of SOFDRA gel is 1 pump per underarm. Do notuse more than 1 pump per underarm, regardless of underarm size.
- Do notuse SOFDRA if the expiration date has passed.
- Do not apply SOFDRA if you:
  - Shaved your underarms or applied deodorant to your armpits within the last 8 hours.
  - Exercised, showered, or washed your underarms within the last 30 minutes.

- Avoid touching the gelwith your hands or fingers.
- Do notget the gel on or near your eyes.
- Always apply and spread SOFDRA gel using the provided Applicator. Do notspread gel with your hands or with a towel.

- Let SOFDRA gel dry for 5 minutesafter it is applied.
  - Do notput on clothing until gel has dried completely.
  - Do notsmoke or go near an open flame until the gel is dry. SOFDRA gel is flammable.
- Do nottouch your underarms after applying the gel.
- Always wash your hands with soap and water right away after applying SOFDRA gelto avoid spreading any gel residue to any other parts of your body.
- Do notshower or wash your underarms for at least 8 hoursafter applying SOFDRA.
- The Bottle contains 30 days of medicine.After applying 30 daily doses of SOFDRA gel, throw away the Blue Cap, Applicator, and Bottle into the household trash.

Prepare to Apply SOFDRA

1 Check if you are ready to apply SOFDRA

1.1Apply SOFDRA before bedtime (Figure B).

1.2 Before applying SOFDRA make sure that you:

Do Notshave your underarms within the last 8 hours,
Do Notapply deodorant to your underarms within the last 8 hours,
Do Notexercise within the last 30 minutes, and
Do Notshower or wash your underarms within the last 30 minutes.

2 Gather supplies

2.1 Gather the following supplies.

- SOFDRA(Figure C)
- Clean towel(Figure D)

3 Check the expiration date

3.1 Check the expiration date("EXP") on the Bottle label to make sure it has not passed (Figure E).

Do notuse SOFDRA if the expiration date has passed.

4 Remove Blue Cap and Applicator from Bottle

4.1 Pullthe Blue Cap straight offthe Bottle and set it aside (Figure F).

4.2 Pullthe gel Applicator straight offthe Bottle and set it aside (Figure G).

5 Prime the pump(First time use only)

Important:Priming the pump is required the first time you use a new Bottle. The purpose of priming is to make sure the pump works correctly and dispenses gel properly.

5.1 Hold the Bottle over a sink.Press the pump all the way down 1 to 2 times, or until you see gel coming out (Figure H).

5.2Use water to wash down any gel in the sink(Figure I).

Do nottouch or use any of the gel residue from the sink.

6 Prepare underarms

6.1 Remove all clothing around both underarms(Figure J).
Note:It is okay to use SOFDRA on underarms with hair or new growth (stubble).

Do notapply SOFDRA to any other part of the body
Do notapply SOFDRA to broken skin.

6.2 Dry both underarms with a clean towelbefore applying SOFDRA gel (Figure K).

Apply 1 Pump of SOFDRA to Each Armpit

7 Apply 1 pump of SOFDRA gel to first underarm

7.1 Hold the Applicator steady and levelwith the top (flat area) pointing up (Figure L).
Put 1 full pump of gel onto the top of the Applicator(Figure L).
Avoidtouching the gel with your hands or fingers.

Do notapply more than 1 pump per underarm, regardless of size.
Do nottilt the Applicator until you apply it to your underarm to avoid spilling the gel.
Do notput the gel inside of the opening at the bottom of the Applicator.

7.2 Spread SOFDRA gel around the whole area of the first underarmusing the Applicator (Figure M).
Alwaysapply and spread SOFDRA gel using the provided Applicator.

Do notspread gel with your hands or with a towel.
Do nottouch your underarms after applying the gel.

8 Apply 1 pump of SOFDRA gel to second underarm

8.1 Hold the Applicator steady and levelwith the top (flat area) pointing up (Figure N).
Put 1 full pump of gel onto the top of the Applicator(Figure N).
Avoidtouching the gel with your hands or fingers.

Do notapply more than 1 pump per underarm, regardless of size.
Do nottilt the Applicator until you apply it to your underarm to avoid spilling the gel.
Do notput the gel inside of the opening at the bottom of the Applicator.

8.2 Spread SOFDRA gel around the whole area of the second underarmusing the Applicator (Figure O).

Alwaysapply and spread SOFDRA gel using the provided Applicator.

Do notspread gel with your hands or with a towel.
Do nottouch your underarms after applying the gel.

9 Let SOFDRA gel dry

9.1 Let SOFDRA gel dry for 5 minutesafter it is applied (Figure P). Keep clothing off the area while it dries.
Note:It is okay to put your arms down.

Do notput on clothing until gel has dried completely.
Do notsmoke or go near an open flame until the gel is dry.
SOFDRA gel is flammable.

What to do After Applying SOFDRA

10 Rinse and dry Applicator

10.1 Rinse off the Applicator with water(Figure Q).
Avoidtouching the gel with your hands or fingers.

10.2 Pat the Applicator dry(Figure R).

11 Wash hands

11.1 Always wash your hands with soap and water right away after applying SOFDRA gelto avoid spreading any gel residue to any other parts of your body (Figure S).

12 Reassemble and store SOFDRA after use

12.1 Push the Applicator straightonto the Bottle, over the pump (Figure T).

12.2 Push the Blue Cap straightonto the top of the Applicator (Figure U).

13 Keep SOFDRA on skin for at least 8 hours

13.1 Wait at least 8 hoursafter applying SOFDRA before you shower or wash your underarms (Figure W).

Do notshower or wash your underarms for at least 8 hours after applying SOFDRA.

Storage Information

Store SOFDRA upright at room temperature between68°F to 77°F (20°C to 25°C) (Figure X)

Keep SOFDRA and all medicines out of reach of children.

Disposal Information

After applying 30 daily doses of SOFDRA gel(Figure Y), throw away the Blue Cap, Applicator, and Bottle into the household trash.

Additional Information

For additional information about how to apply SOFDRA, go to www.sofdra.com or call 1-866-763-6337

Manufactured For:
Botanix SB Inc.
Phoenix, AZ 85016

SOFDRA™ is a trademark of Botanix SB Inc.

This Instructions for Use has been approved by the U.S. Food and Drug Administration.
Issued: 07/2025

PRINCIPAL DISPLAY PANEL - 50 mL Bottle Carton

NDC 83723-010-50
Rx Only

Sofdra™
(sofpironium) topical gel, 12.45%

For topical use only.

Apply before bed.

Wash hands with soap and
water immediately after use.

STOP
You MUST read
the Instructions
for Use

Each pump actuation delivers
0.67 mL of gel containing 72 mg
of sofpironium.

Net quantity
50 mL multi-dose metered
pump capable of dispensing 60
pump actuations.